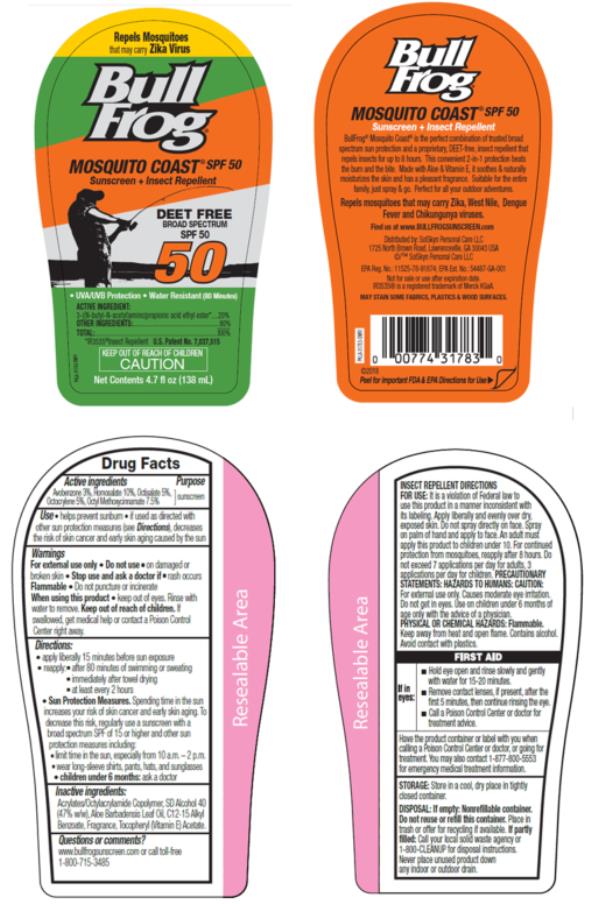 DRUG LABEL: Bull Frog Mosquito Coast SPL 50 Pump
NDC: 70281-314 | Form: SPRAY
Manufacturer: SolSkyn Personal Care LLC
Category: otc | Type: HUMAN OTC DRUG LABEL
Date: 20181105

ACTIVE INGREDIENTS: AVOBENZONE 3 g/100 g; HOMOSALATE 10 g/100 g; OCTISALATE 5 g/100 g; OCTOCRYLENE 5 g/100 g; OCTINOXATE 7.5 g/100 g
INACTIVE INGREDIENTS: ALCOHOL; ALOE VERA LEAF; ALKYL (C12-15) BENZOATE; .ALPHA.-TOCOPHEROL ACETATE

Bull Frog Mosquito Coast Broad Spectrum Pump Spray SPF 50

Item Number: 31783-700-DM06

NDC Number: 70281-314-12

Product Name: Bull Frog Mosquito Coast SPF 50 Pump

Active Ingredients

Avobenzone 3%, Homosalate 10%, Octisalate 5%, Octocrylene 5%, Octyl Methoxycinnamate 7.5%

Purpose

Sunscreen

Use

- helps prevent sunburn

Warnings

Skin Cancer/Skin Aging Alert: Spending time in the sun increases your risk of skin cancer and early skin aging. This product has been shown only to prevent sunburn, not skin cancer or early skin aging.

• For external use only

• Do not use

on damaged or broken skin.

• When using this product

keep out of eyes. Rinse with water to remove.

• Stop use and ask a doctor if

rash occurs.

• Flammable: • do not puncture or incinerate

• Keep out of reach of children.

If swallowed, get medical help or contact a Poison Control Center right away.

Directions

- apply liberally 15 minutes before sun exposure
- re-apply:
  • after 80 minutes of swimming or sweating
  • immediately after towel drying
  • at least every 2 hours
- children under 6 months: ask a doctor

Other information

- protect the product in this container from excessive heat and direct sun

Inactive Ingredients

Acrylates/Octylacrylamide Copolymer, SD Alcohol 40 (47% w/w), Aloe Barbadensis Leaf Oil, C12-15 Alkyl Benzoate, Fragrance, Tocopheryl (Vitamin E) Acetate

Questions or comments?

www.bullfrogsunscreen.com or call toll-free 1-800-715-3485

INSECT REPELLENT DIRECTIONS FOR USE: It is a violation of Federal law to use this product in a manner inconsistent with its labeling. Apply liberally and evenly over dry, exposed skin. Do not spray directly on face. Spray on palm of hand and apply to face. An adult must apply this product to children under 10. For continued protection from mosquitoes, re-apply after 8 hours. Do not exceed 7 applications per day for adults, 3 applications per day for children.

PRECAUTIONARY STATEMENTS: HAZARDS TO HUMANS: CAUTION: For external use only. Causes moderate eye irritation. Do not get in eyes. Use on children under 6 months of age only with the advice of a physician.

PHYSICAL OR CHEMICAL HAZARDS: Flammable. Keep away from heat and open flame. Contains alcohol. Avoid contact with plastics.

FIRST AID

If in eyes:

- Hold eye open and rinse slowly and gently with water for 15-20 minutes.
- Remove contact lenses, if present, after the first 5 minutes, then continue rinsing the eye.
- Call a poison control center or doctor for treatment advice.

Have the product container or label with you when calling a poison control center or doctor, or going for treatment. You may also contact 1-877-800-5553 for emergency medical treatment information.

STORAGE:

Store in a cool, dry place in tightly closed container.

DISPOSAL: Do not Puncture or Incinerate! If empty: Nonrefillable container. Do not reuse or refill this container. Place in trash or offer for recycling if available. If partly filled: Call your local solid waste agency or 1-800-CLEANUP for disposal instructions.

MAY STAIN SOME FABRICS, PLASTICS AND WOOD SURFACES.

EPA Reg. No.: 11525-78-91874

EPA Est. No.: 54487-GA-001

PRINCIPAL DISPLAY PANEL

Bull
Frog
Mosquito Coast SPF 50
Sunscreen + Insect Repellent